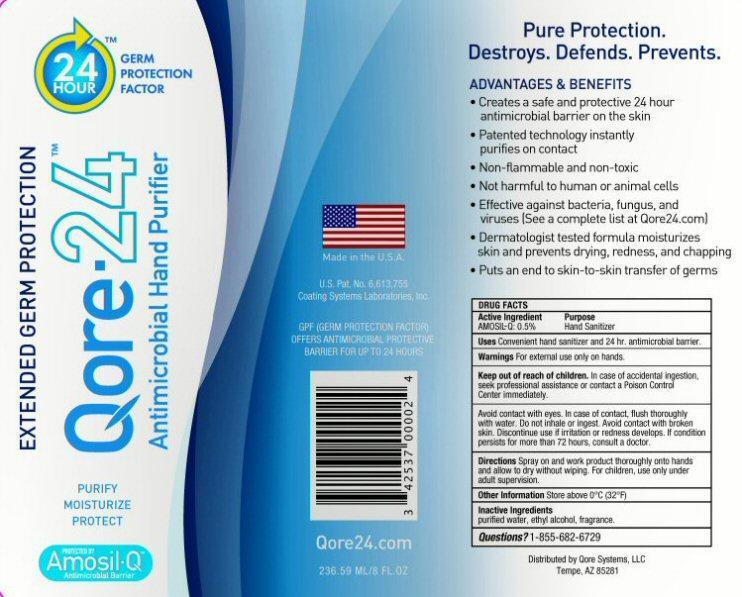 DRUG LABEL: Qore 24
NDC: 42537-024 | Form: SPRAY
Manufacturer: Qore Systems LLC
Category: otc | Type: HUMAN OTC DRUG LABEL
Date: 20120814

ACTIVE INGREDIENTS: BENZALKONIUM CHLORIDE 10 mg/100 mL
INACTIVE INGREDIENTS: WATER; ALCOHOL; DIMETHYLOCTADECYL(3-(TRIMETHOXYSILYL)PROPYL)AMMONIUM CHLORIDE

Active Ingredient Section

DRUG FACTS

Active Ingredient

AMOSIL-Q 0.5% - Benzalkonium Chloride 0.10%

Purpose Section

Purpose Hand Sanitizer

Keep Out of Reach of Children Section

Keep out of reach of children. In case of accidental ingestion, seek professional assistance or contact a Poison Control Center immediately.

Uses Section

Uses Convenient hand sanitize and 24 hr. antimicrobial barrier.

Warnings Section

Warnings For external use only on hands. In case of accidental ingestion, seek professional assistance or contact a Poison Control Center immediately.

Avoid contact with eyes. In case of contact, flush thoroughly with water. Do not inhale or ingest. Avoid contact with broken skin. Discontinue use if irritation or redness developes. If condition persists for more than 72 hours, consult a doctor.

Directions Section

Directions Spray on and work product thoroughly onto hands and allow to dry without wiping. For children, use only under adult supervision.

Other Information and Questions Section

Other Information Store above 0 degrees C (32 degrees F)

Questions? 1-800-950-7885

Inactive Ingredients Section

Inactive ingredients

purified water, ethylalcohol, fragrance, (3-(Trimethoxysil)Propyl)OctadecyDimethylAmmonium Chloride 0.4%

Package Label Section Qore-24

24 HOUR tm GERM PROTECTION FACTOR

EXTENDED GERM PROTECTION Qore-24 tm Antimicrobial Hand Purifier PURIFY MOISTURIZE PROTECT

PROTECTED BY Amosil-Q Antimicrobial Barrier

Qore24.com U.S.Pat. No. 6,613,755 Coating Systems Laboratories, Inc. Made in the U.S.A.

GPF (GERM PROTECTION FACTOR) OFFERS ANTIMICROBIAL PROTECTIVE BARRIERFOR UP TO 24 HOURS Qore24.com

Pure Protection, Destroys, Defends, Prevents,

ADVANTAGES and BENEFITS

- Creates a safe and protective 24 hour antimicrobial barrier on the skin
- Patented technology instantly purifies on contact
- Non-flammable and non-toxic
- Not harmful to human or animal cells
- Effective against bacteria, fungus, and viruses (See a complete list at Qore24.com)
- Dermatologist tested formula moisturizes skin and prevents drying, redness, and chapping
- Puts an end to skin-to-skin transfer of germs

Distributed by Qore Systems, LLC Tempe, AZ 85281